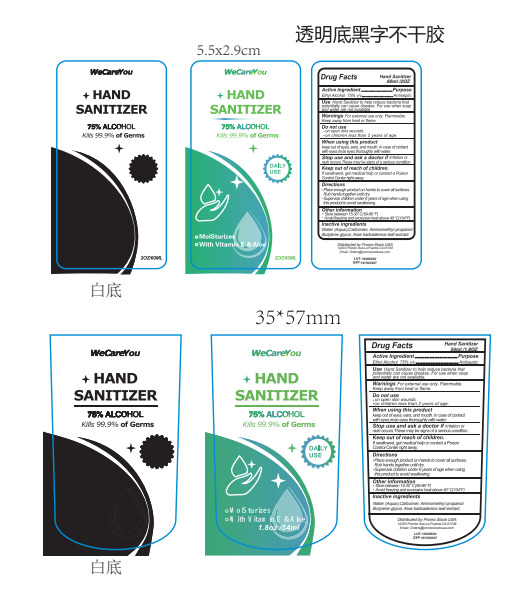 DRUG LABEL: Hand Sanitizer
NDC: 75541-015 | Form: GEL
Manufacturer: NINGBO MEITELI COSMETICS CO., LTD
Category: otc | Type: HUMAN OTC DRUG LABEL
Date: 20240918

ACTIVE INGREDIENTS: ALCOHOL 75 mL/100 mL
INACTIVE INGREDIENTS: CARBOXYPOLYMETHYLENE; WATER; BUTYLENE GLYCOL; ALOE VERA LEAF; AMINOMETHYLPROPANOL

75541-015

Active Ingredient(s)

ETHYL ALCOHOL 75%

Purpose

Antiseptic

Use

Use Hand Sanitizer to help reduce bacteria that potentially can cause disease. For use when soap and water are not available.

Warnings

Warnings For external use only. Flammable. Keep away from heat or flame.

Do not use

●on open skin wounds.
●on children less than 2 years of age.

When using this product keep out of eyes, ears, and mouth. In case of contact with eyes,ninse eyes thoroughly with water.

Stop use and ask a doctor if imitation or rash occurs. These may be signs of a serious condition.

Keep out of reach of children. If swallowed, get medical help or contact a Poison Control Center right away.

Directions

●Place enough product on hands to cover all surfaces. Rub hands together until dry.
●Supervise children under 6 years of age when using this product to avoid swallowing.

Other information

1.Store between 15-30"C(59-86*F)
2.Avoid freezing and excessive heat above 40°C(104°F)

Inactive ingredients

Water (Aqua),Carbomer, Aminomethyl propanol Butylene glycol, Aloe barbadensis leaf extract